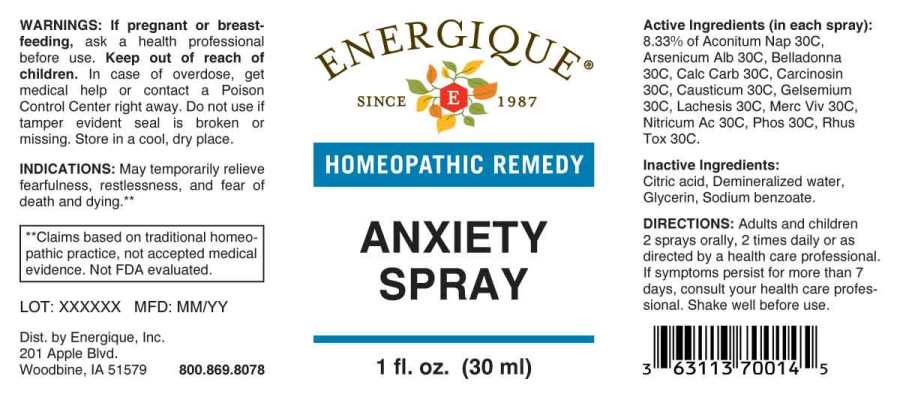 DRUG LABEL: Anxiety
NDC: 44911-0038 | Form: SPRAY
Manufacturer: Energique, Inc.
Category: homeopathic | Type: HUMAN OTC DRUG LABEL
Date: 20231107

ACTIVE INGREDIENTS: ARSENIC TRIOXIDE 30 [hp_C]/1 mL; ACONITUM NAPELLUS 30 [hp_C]/1 mL; ATROPA BELLADONNA 30 [hp_C]/1 mL; OYSTER SHELL CALCIUM CARBONATE, CRUDE 30 [hp_C]/1 mL; HUMAN BREAST TUMOR CELL 30 [hp_C]/1 mL; CAUSTICUM 30 [hp_C]/1 mL; GELSEMIUM SEMPERVIRENS ROOT 30 [hp_C]/1 mL; LACHESIS MUTA VENOM 30 [hp_C]/1 mL; MERCURY 30 [hp_C]/1 mL; NITRIC ACID 30 [hp_C]/1 mL; PHOSPHORUS 30 [hp_C]/1 mL; TOXICODENDRON PUBESCENS LEAF 30 [hp_C]/1 mL
INACTIVE INGREDIENTS: ANHYDROUS CITRIC ACID; GLYCERIN; SODIUM BENZOATE; WATER

Drug Facts:

ACTIVE INGREDIENTS:

(in each spray): 8.33% of Aconitum Napellus 30C, Arsenicum Album 30C, Belladonna 30C, Calcarea Carbonica 30C, Carcinosin 30C, Causticum 30C, Gelsemium Sempervirens 30C, Lachesis Mutus 30C, Mercurius Vivus 30C, Nitricum Acidum 30C, Phosphorus 30C, Rhus Tox 30C.

INDICATIONS:

May temporarily relieve fearfulness, restlessness, and fear of death and dying.**

**Claims based on traditional homeopathic practice, not accepted medical evidence. Not FDA evaluated.

WARNINGS:

If pregnant or breast-feeding, ask a health professional before use.

Keep out of reach of children. In case of overdose, get medical help or contact a Poison Control Center right away.

Do not use if tamper evident seal is broken or missing. Store in a cool, dry place.

DIRECTIONS:

Adults and children 2 sprays orally, 2 times daily or as directed by a health care professional. If symptoms persist for more than 7 days, consult your health care professional. Shake well before use.

INACTIVE INGREDIENTS:

Citric Acid, Demineralized Water, Glycerin, Sodium Benzoate.

Keep out of reach of children. In case of overdose, get medical help or contact a Poison Control Center right away.

INDICATIONS:

May temporarily relieve fearfulness, restlessness, and fear of death and dying.**

**Claims based on traditional homeopathic practice, not accepted medical evidence. Not FDA evaluated.

QUESTIONS:

Dist. by Energique, Inc.

201 Apple Blvd.

Woodbine, IA 51579

800.869.8078

PACKAGE LABEL DISPLAY:

ENERGIQUE

SINCE 1987

HOMEOPATHIC REMEDY

ANXIETY SPRAY

1 fl. oz. (30 ml)